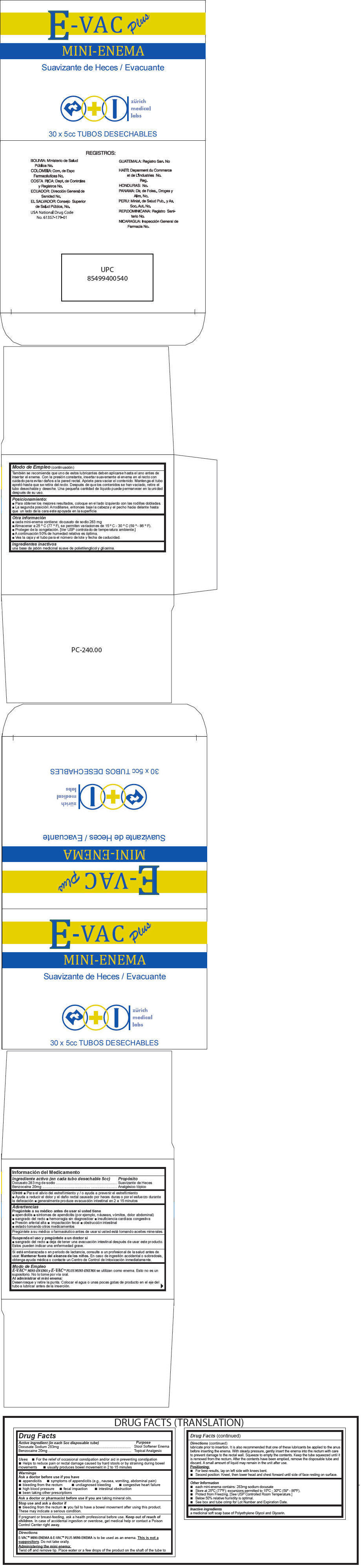 DRUG LABEL: E-Vac Plus
NDC: 61357-179 | Form: ENEMA
Manufacturer: ZURICH MEDICAL LABS, LLC
Category: otc | Type: HUMAN OTC DRUG LABEL
Date: 20140321

ACTIVE INGREDIENTS: DOCUSATE SODIUM 283 mg/5 mL; BENZOCAINE 20 mg/5 mL
INACTIVE INGREDIENTS: POLYETHYLENE GLYCOLS; GLYCERIN

E-Vac Plus

Drug Facts

ACTIVE INGREDIENT

Active ingredient (in each 5cc disposable tube) | Purpose
Docusate Sodium 283mg | Stool Softener Enema
Benzocaine 20mg | Topical Analgesic

Uses

- For the relief of occasional constipation and/or aid in preventing constipation
- Helps to reduce pain or rectal damage caused by hard stools or by straining during bowel movements
- usually produces bowel movement in 2 to 15 minutes

Warnings

Ask a doctor before use if you have

- appendicitis
- symptoms of appendicitis (e.g., nausea, vomiting, abdominal pain)
- bleeding from the rectum
- undiagnosed bleeding
- congestive heart failure
- high blood pressure
- fecal impaction
- intestinal obstruction
- been taking other prescriptions

Ask a doctor or pharmacist before use if you are taking mineral oils.

Stop use and ask a doctor if

- bleeding from the rectum
- you fail to have a bowel movement after using this product.

These may indicate a serious condition.

PREGNANCY OR BREAST FEEDING

If pregnant or breast-feeding, ask a health professional before use.

Keep out of reach of children. In case of accidental ingestion or overdose, get medical help or contact a Poison Control Center right away.

Directions

E-VAC™ MINI-ENEMA & E-VAC™ PLUS MINI-ENEMA is to be used as an enema. This is not a suppository. Do not take orally.

Administering the mini enema

Twist off and remove tip. Place water or a few drops of the product on the shaft of the tube to lubricate prior to insertion. It is also recommended that one of these lubricants be applied to the anus before inserting the enema. With steady pressure, gently insert the enema into the rectum with care to prevent damage to the rectal wall. Squeeze to empty the contents. Keep the tube squeezed until it is removed from the rectum. After the contents have been emptied, remove the disposable tube and discard. A small amount of liquid may remain in the unit after use.

Positioning

- For best results, lay on left side with knees bent.
- Second position: Kneel, then lower head and chest forward until side of face resting on surface.

Other Information

- each mini-enema contains: 283mg sodium docusate
- Store at 25°C (77°F); excursions permitted to 15°C - 30°C (59° - 86°F).
- Protect from Freezing. [See USP Controlled Room Temperature.]
- Below 50% relative humidity is optimal.
- See box and tube crimp for Lot Number and Expiration Date.

Inactive ingredients

a medicinal soft soap base of Polyethylene Glycol and Glycerin.

PRINCIPAL DISPLAY PANEL - 30 Tube Box

E-VAC
Plus

MINI-ENEMA

Suavizante de Heces / Evacuante

zürich
medical
labs

30 x 5cc TUBOS DESECHABLES